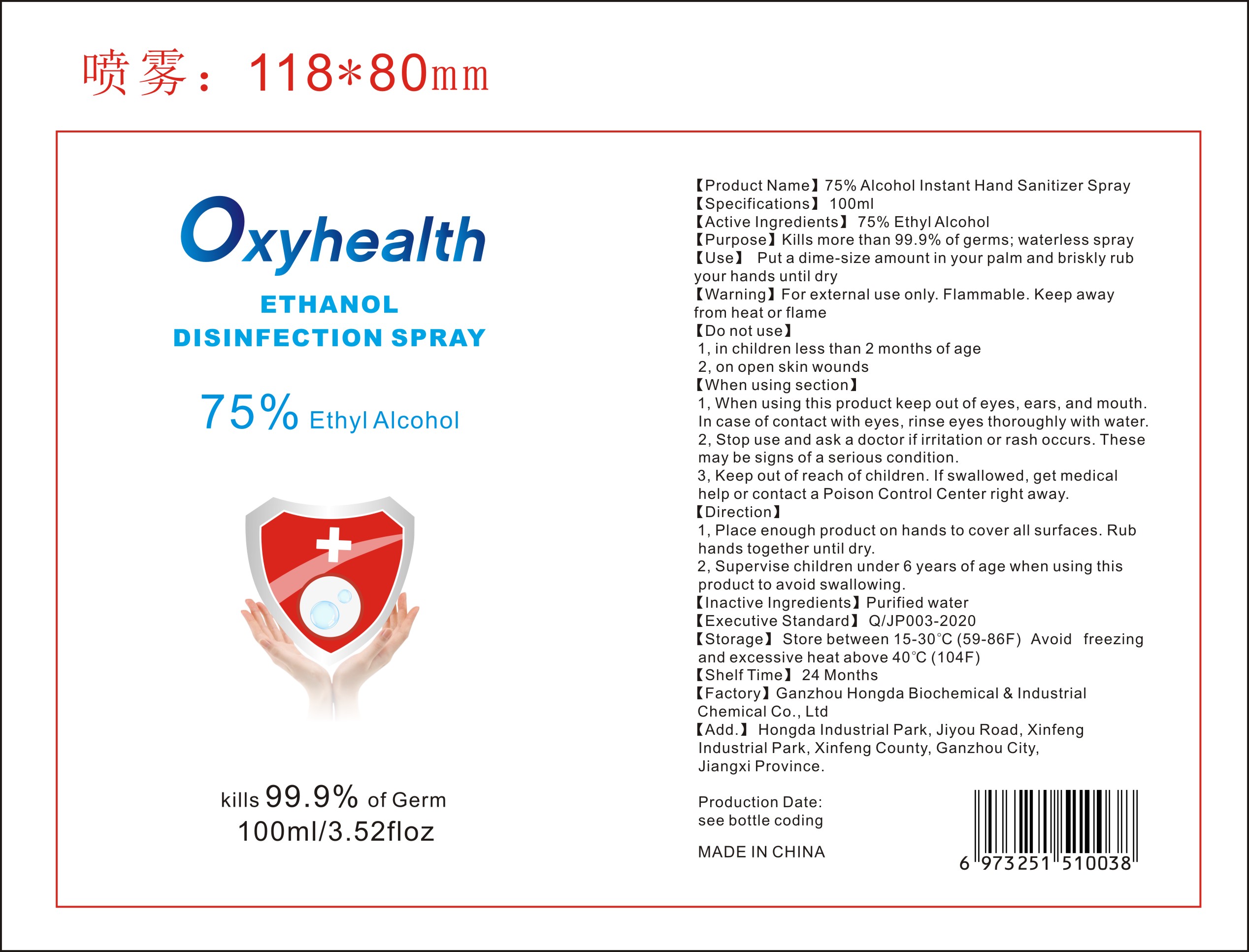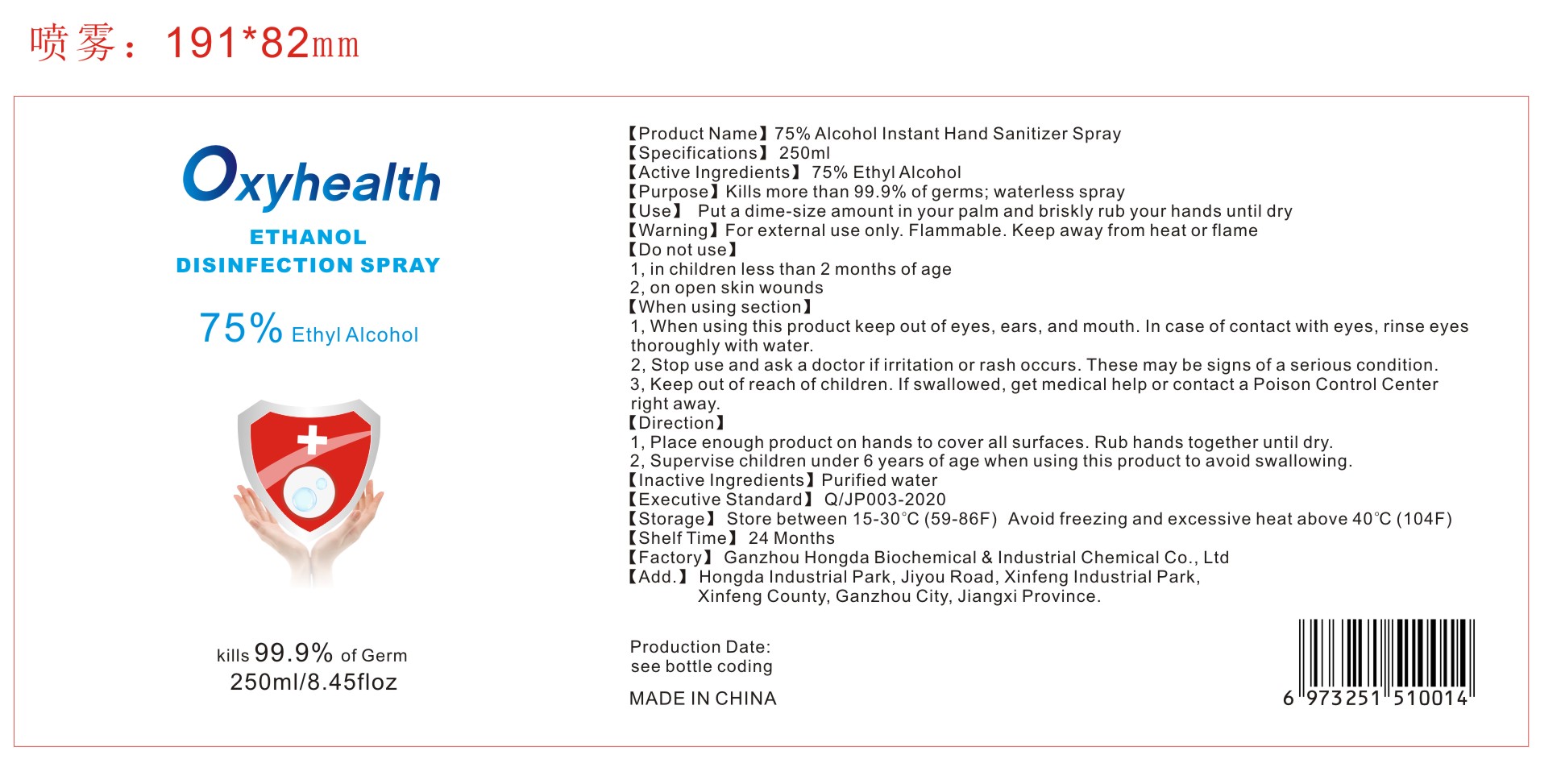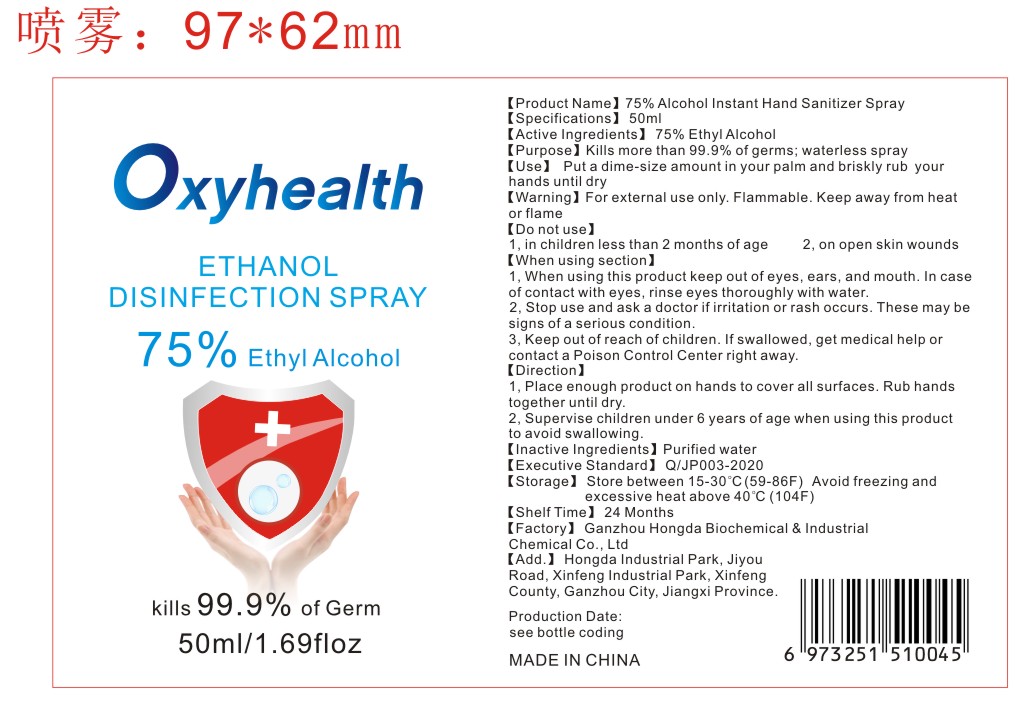 DRUG LABEL: 75% Alcohol Instant Hand Sanitizer
NDC: 78412-006 | Form: SPRAY
Manufacturer: Ganzhou Hongda Biochemical and Industrial   Chemical Co., Ltd
Category: otc | Type: HUMAN OTC DRUG LABEL
Date: 20200528

ACTIVE INGREDIENTS: ALCOHOL 75 mL/100 mL
INACTIVE INGREDIENTS: WATER

75% Alcohol Instant Hand Sanitizer Spray

Active Ingredient(s)

75% Ethyl alcohol

Purpose

Kills more than 99.9% of germs; waterless gel

Use

Put a dime-size amount in your palm and briskly rub your hands until dry

Warnings

For external use only. Flammable. Keep away from

heat or flame

Do not use

1, In children less than 2 months of age.
2, On open skin wounds.

WHEN USING

1, When using this product keep out of eyes, ears, and mouth. In case of contact with eyes, rinse eyes thoroughly with water.
2, Stop use and ask a doctor if irritation or rash occurs. These may be signs of a serious condition.
3, Keep out of reach of children. If swallowed, get medical help or contact a Poison Control Center right away.

Stop use and ask a doctor if irritation or rash occurs. These may be signs of a serious condition.

Keep out of reach of children. If swallowed, get medical help or contact a Poison Control Center right away.

Directions

1, Place enough product on hands to cover all surfaces. Rub hands together until dry.
2, Supervise children under 6 years of age when using this product to avoid swallowing.

Other information

- Store between 15-30C (59-86F)
- Avoid freezing and excessive heat above 40C (104F)

Inactive ingredients

purified water